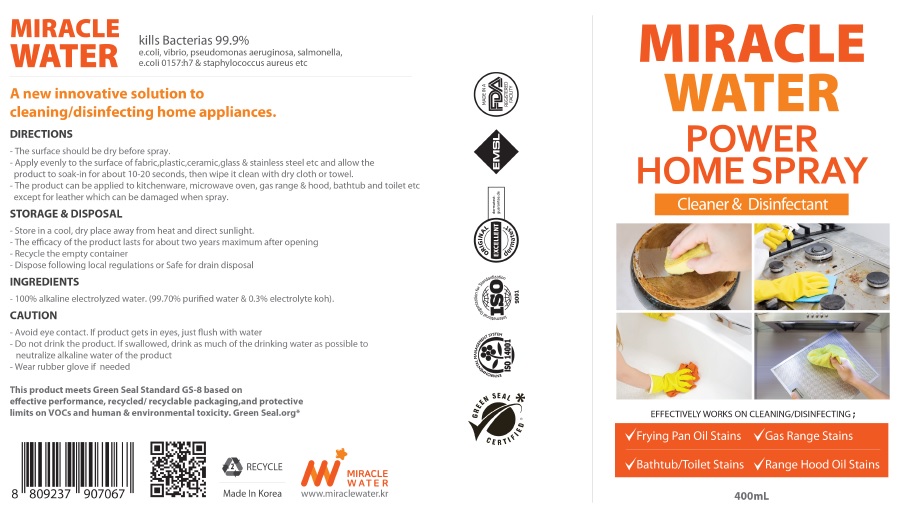 DRUG LABEL: MIRACLE WATER 3 in 1
NDC: 79659-001 | Form: SPRAY
Manufacturer: ORIGIN G&B CO.,LTD
Category: otc | Type: HUMAN OTC DRUG LABEL
Date: 20200709

ACTIVE INGREDIENTS: POTASSIUM HYDROXIDE 0.3 mg/1 mL
INACTIVE INGREDIENTS: WATER

MIRACLE WATER 3 in 1

Active Ingredients

Potassium hydroxide

Purpose

Cleaner, Disinfectant & Deodorization

Warnings

Avoid eye contact. If product gets in eyes, just flush with water

Do not drink the product.

If swallowed, drink as much of the drinking water as possible to neutralize alkaline water of the product, and go to the nearest medical hospital

Wear rubber glove if needed

Uses

cleaning, disinfection, deodorization

Direction

surface should be dry before spray.

Apply evenly to the surface and allow the product to spray for about 10-20 seconds, then wipe it clean with dry cloth or towel.

Product can be applied to fabric, furnishings, tile, ceramic, glass, stainless steel&amp; pet supplies etc.

Store in a cool, dry place away from heat and direct sunlight.

The efficacy of the product lasts for about six months maximum after opening.

Recycle the empty container.

Dispose following local regulations or Safe for drain disposal.

Inactive Ingredients

Water